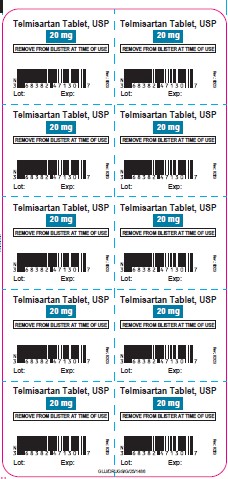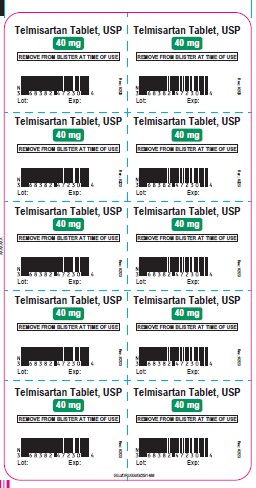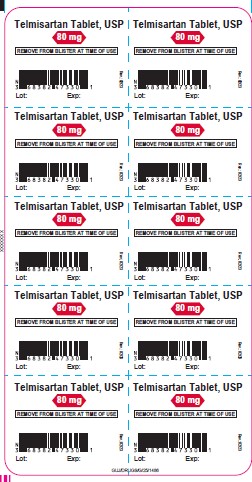 DRUG LABEL: telmisartan
NDC: 65841-804 | Form: TABLET
Manufacturer: Zydus Lifesciences Limited
Category: prescription | Type: HUMAN PRESCRIPTION DRUG LABEL
Date: 20240812

ACTIVE INGREDIENTS: TELMISARTAN 20 mg/1 1
INACTIVE INGREDIENTS: FERRIC OXIDE RED; LACTOSE MONOHYDRATE; MAGNESIUM STEARATE; MEGLUMINE; POVIDONE; SODIUM HYDROXIDE; SODIUM STEARYL FUMARATE; SORBITOL

TELMISARTAN TABLETS

PACKAGE LABEL.PRINCIPAL DISPLAY PANEL

NDC 65841-804-30 in blister pack of 10 tablets

Telmisartan Tablets USP, 20 mg

Rx only

10 tablets

NDC 65841-805-30 in blister pack of 10 tablets

Telmisartan Tablets USP, 40 mg

Rx only

10 tablets

NDC 65841-806-30 in blister pack of 10 tablets

Telmisartan Tablets USP, 80 mg

Rx only

10 tablets